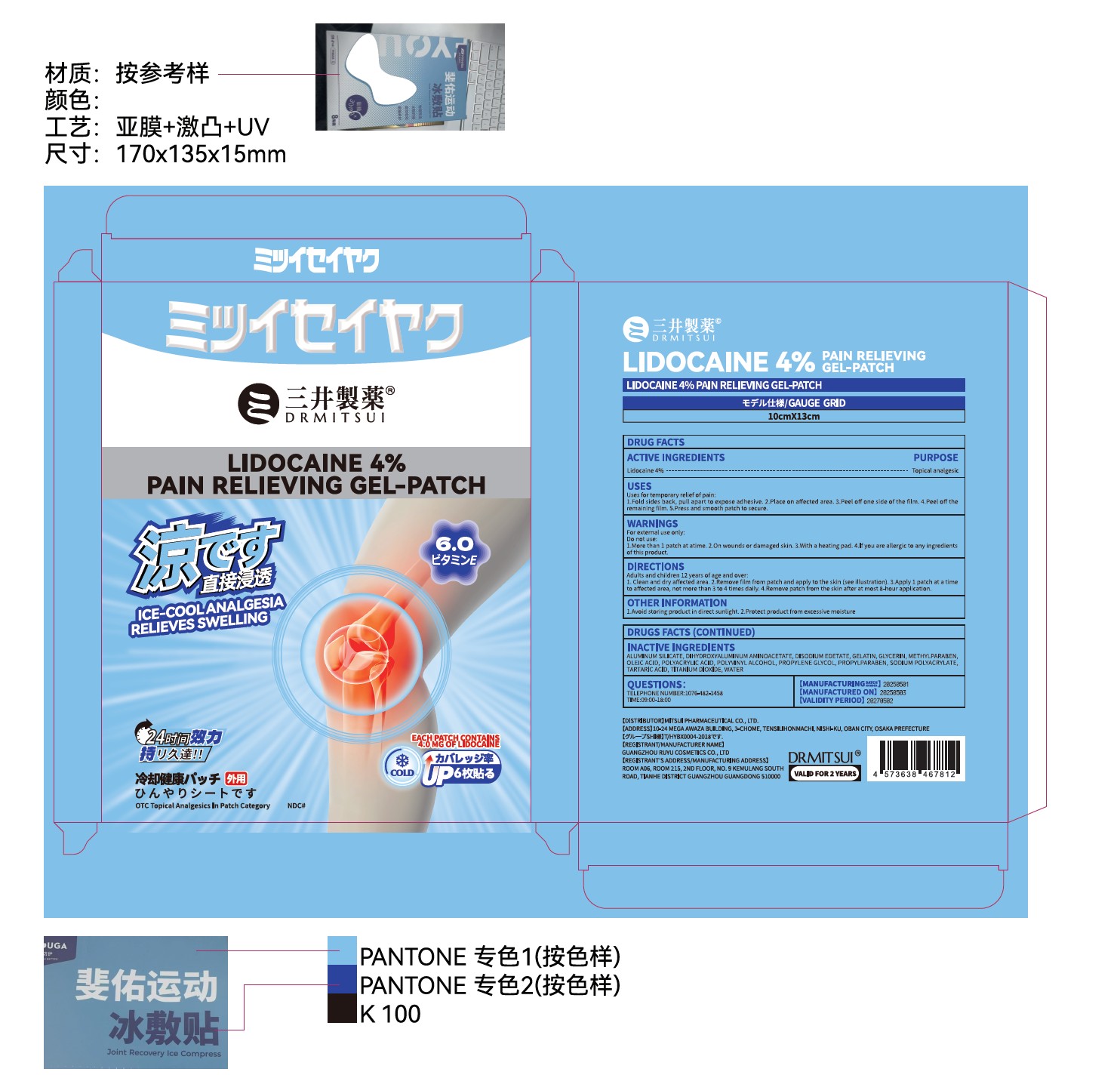 DRUG LABEL: DRMITSUI Lidocaine 4% Pain Relieving Gel
NDC: 85713-102 | Form: PATCH
Manufacturer: Guangzhou Ruyu Cosmetics Co., Ltd
Category: otc | Type: HUMAN OTC DRUG LABEL
Date: 20251216

ACTIVE INGREDIENTS: LIDOCAINE 4 g/100 g
INACTIVE INGREDIENTS: SODIUM POLYACRYLATE (8000 MW); PROPYLENE GLYCOL; POLYACRYLIC ACID (8000 MW); POLYVINYL ALCOHOL; TARTARIC ACID; DIHYDROXYALUMINUM AMINOACETATE ANHYDROUS; ALUMINUM SILICATE; WATER; TITANIUM DIOXIDE; METHYLPARABEN; PROPYLPARABEN; GELATIN; GLYCERIN; EDETATE DISODIUM

ACTIVE INGREDIENT

Lidocaine 4% ----
PURPOSE
Topical analgesic

Keep out of reach of children

PURPOSE

Uses for temporary relief of pain:
1.Fold sides back, pull apart to expose adhesive. 2.Place on affected area. 3.Peel off one side of the film. 4.Peel off the
remaining film.5.Press and smooth patch to secure.

WARNINGS

For external use only

Do not use:
1.More than 1 patch at atime. 2.0n wounds or damaged skin. 3.With a heating pad. 4.lf you are allergic to any ingredients
of this product.

DOSAGE AND ADMINISTRATION

Apply 1 patch at a time
to affected area, not more than 3 to 4 times daily

INDICATIONS AND USAGE

Adults and children 12 years of age and over:
1. Clean and dry affected area. 2.Remove film from patch and apply to the skin (see illustration). 3.Apply 1 patch at a time
to affected area, not more than 3 to 4 times daily. 4.Remove patch from the skin after at most 8-hour application.

INACTIVE INGREDIENTS
ALUMINUM SILICATE, DIHYDROXYALUMINUM AMINOACETATE, DISODIUM EDETATE, GELATIN, GLYCERIN, METHYLPARABENOLEIC ACID, POLYACRYLIC ACID, POLYVINYL ALCOHOL, PROPYLENE GLYCOL, PROPYLPARABEN, SODIUM POLYACRYLATETARTARIC ACID, TITANIUM DIOXIDE, WATER